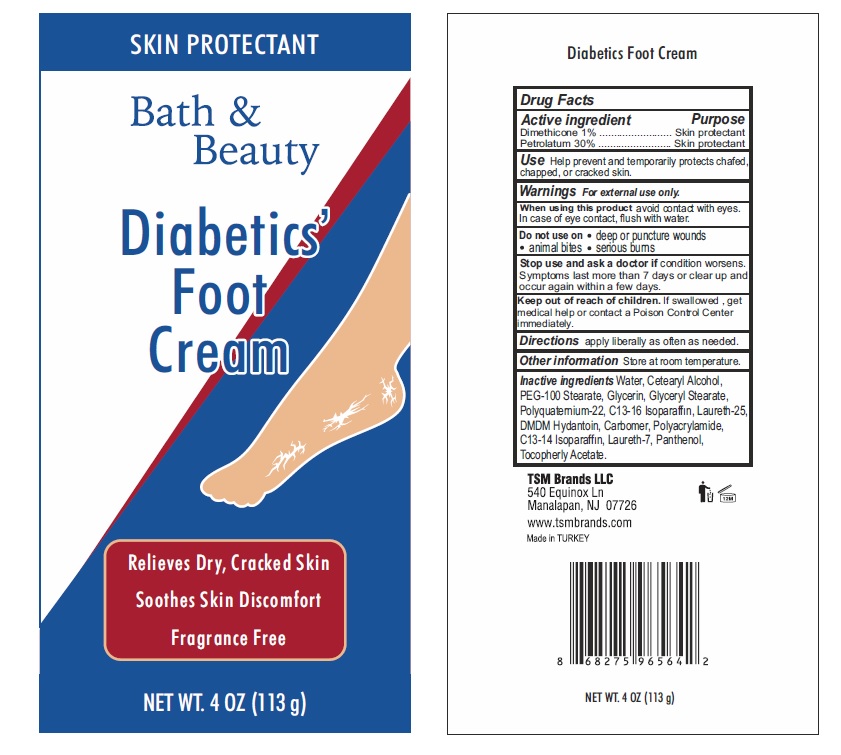 DRUG LABEL: Bath and beauty
NDC: 76772-026 | Form: LOTION
Manufacturer: TSM ITHALAT IHRACAT SANAYI VE DIS TICARET LIMITED SIRKETI
Category: otc | Type: HUMAN OTC DRUG LABEL
Date: 20210310

ACTIVE INGREDIENTS: PETROLATUM 30 g/100 g; DIMETHICONE 1 g/100 g
INACTIVE INGREDIENTS: GLYCERYL MONOSTEARATE; WATER; GLYCERIN; POLYACRYLAMIDE (1500 MW); DMDM HYDANTOIN; C13-16 ISOPARAFFIN; LAURETH-7; POLYQUATERNIUM-22 (4500 MPA.S); .ALPHA.-TOCOPHEROL ACETATE, D-; CETOSTEARYL ALCOHOL; CARBOXYPOLYMETHYLENE; PANTHENOL; PEG-100 STEARATE; LAURETH-25; C13-14 ISOPARAFFIN

Bath & Beauty Diabetics' Foot Cream

Active Ingredient Purpose

Dimethicone 1% ...... Skin Protectant

Petrolatum 30%........Skin Protectant

PURPOSE

Skin protectant

Keep out of reach of children. If swallowed, get medical help or contact a Poison Control Center immediately.

INDICATIONS AND USAGE

Use help prevent and temporarily protets chafed, chapped, or cracked skin.

Warnings For external use only.

When using this product

avoid contact with eyes. In case of eye contact, flush with water.

Do not use on

deep or puncture wounds
animal bites
serious burns

Stop use and ask a doctor if condition worsens. Symptoms last more than 7 days or clear up and occur again within a few days.

DOSAGE AND ADMINISTRATION

Directions apply liberally as often as needed.

Other information Store at room temperature.

INACTIVE INGREDIENT

Inactive Ingredients Water, Ceterayl Alcohol, PEG-100 Stearate, Glycerin, Glyceryl Stearate, Polyquaternium-22, C13-16 Isoparaffin Laureth-25,DMDM Hydantoin, Carbomer, Polyacrylamide, C13-14 Isoparaffin, Laureth-7, Panthenol, Tocopheryl Acetate